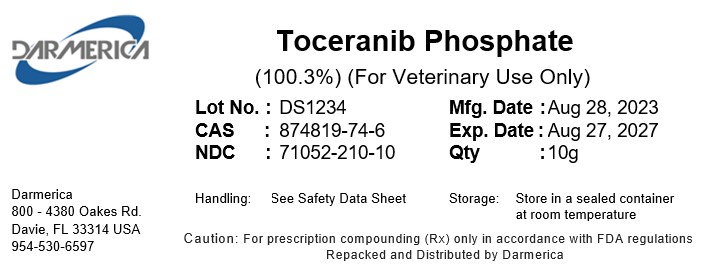 DRUG LABEL: Toceranib phosphate
NDC: 71052-210 | Form: POWDER
Manufacturer: DARMERICA, LLC
Category: other | Type: BULK INGREDIENT - ANIMAL DRUG
Date: 20250220

ACTIVE INGREDIENTS: Toceranib phosphate 1 kg/1 kg

Toceranib phosphate